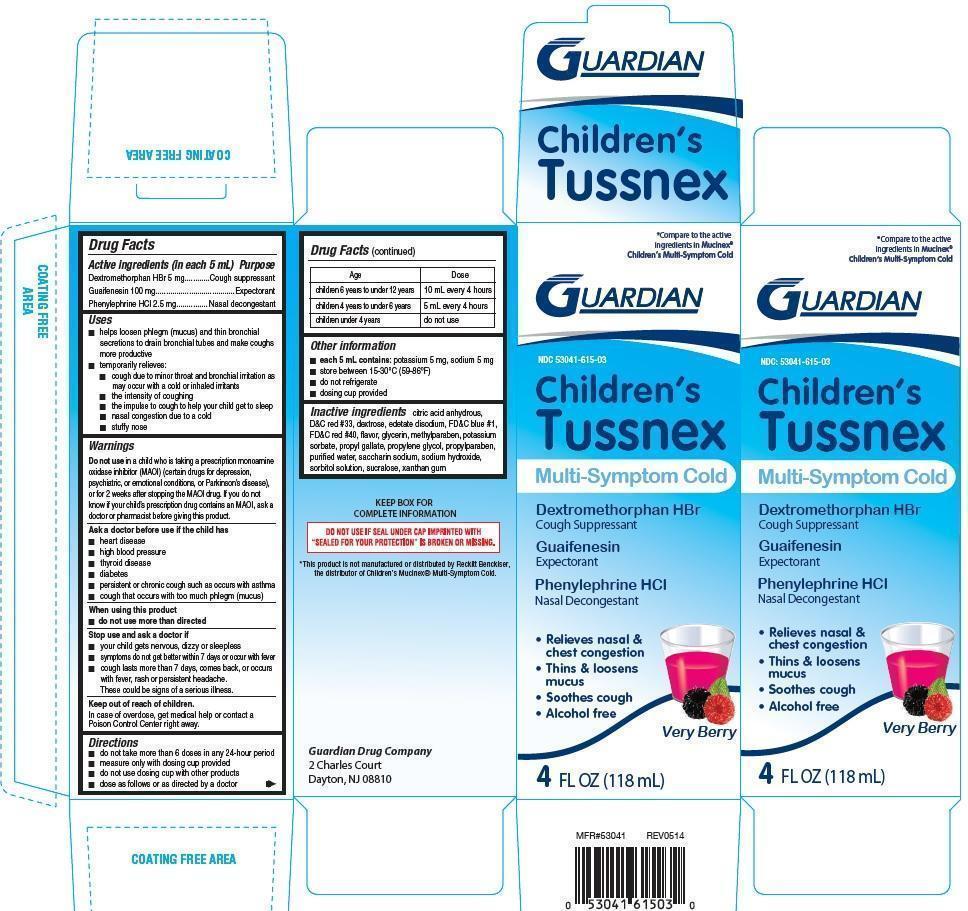 DRUG LABEL: Childrens Tussnex Multi-symptom cold
NDC: 53041-615 | Form: LIQUID
Manufacturer: Guardian Drug Company
Category: otc | Type: HUMAN OTC DRUG LABEL
Date: 20241219

ACTIVE INGREDIENTS: DEXTROMETHORPHAN HYDROBROMIDE 5 mg/5 mL; GUAIFENESIN 100 mg/5 mL; PHENYLEPHRINE HYDROCHLORIDE 2.5 mg/5 mL
INACTIVE INGREDIENTS: ANHYDROUS CITRIC ACID; D&C RED NO. 33; DEXTROSE; EDETATE DISODIUM; FD&C BLUE NO. 1; FD&C RED NO. 40; GLYCERIN; METHYLPARABEN; POTASSIUM SORBATE; PROPYL GALLATE; PROPYLENE GLYCOL; PROPYLPARABEN; SACCHARIN SODIUM; WATER; SODIUM HYDROXIDE; SORBITOL; SUCRALOSE; XANTHAN GUM

Childrens Tussnex Multi-symptom cold

Active ingredients (in each 5 mL)

Dextromethorphan HBr 5 mg

Guaifenesin 100 mg

Phenylephrine HCl 2.5 mg

Purpose

Cough suppressant

Expectorant

Nasal decongestant

Uses

- helps loosen phlegm (mucus) and thin bronchial secretions to drain bronchial tubes and make coughs more productive
- temporarily relieves:
- cough due to minor throat and bronchial irritation as may occur with a cold or inhaled irritants
- the intensity of coughing
- the impulse to cough to help your child get to sleep
- nasal congestion due to a cold
- stuffy nose

Warnings

Do not use in a child who is taking a prescription monoamine oxidase inhibitor (MAOI)(certain drugs for depression, psychiatric, or emotional conditions, or Parkinson's disease), or for 2 weeks after stopping the MAOI drug. If you do not know if your prescription drug contains an MAOI, ask a doctor or pharmacist before giving this product.

Ask a doctor before use if the child has

- heart disease
- high blood pressure
- thyroid disease
- diabetes
- persistent or chronic cough such as occurs with asthma
- cough that occurs with too much phlegm (mucus)

When using this product

- do not use more than directed

Stop use and ask a doctor if

- your child gets nervous, dizzy or sleepless
- symptoms do not get better within 7 days or occur with fever
- cough lasts more than 7 days, comes back, or occurs with fever, rash or persistent headache. These could be signs of a serious illness.

keep out of reach of children. In case of overdose, get medical help or contact a poison control center right away.

Directions

- do not take more than 6 doses in any 24 hour period
- measure only with dosing cup provided
- do not use dosing cup with other products
- dose as follows or as directed by a doctor

Age | Dose
children 6 years to under 12 years | 10 mL every 4 hours
children 4 years to under 6 years | 5 mL every 4 hours
children under 4 years | do not use

Other information

- each 5 mL contains: potassium 5 mg, sodium 5 mg
- store between 15-30oC (59-86oF)
- do not refrigerate
- dosing cup provided

Inactive ingredients

citric acid anhydrous, D and C red 33, dextrose, edetate disodium, FD and C blue 1, FD and C red 40, flavor, glycerin, methylparaben, potassium sorbate, propyl gallate, propylene glycol, propylparaben, purified water, saccharin sodium, sodium hydroxide, sorbitol solution, sucralose, xanthan gum

PDP

compare to active ingredients in Mucinex children's Multi-symptom cold

Children's Tussnex Multi-symptom cold

Dextromethorphan HBr

Cough suppressant

Guaifenesin

Expectorant

Phenylephrine HCl

Nasal decongestant

Relieves nasal and chest chest congestion

Thins and loosens mucus

Soothes cough

Alcohol free